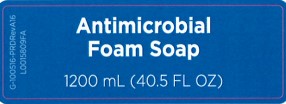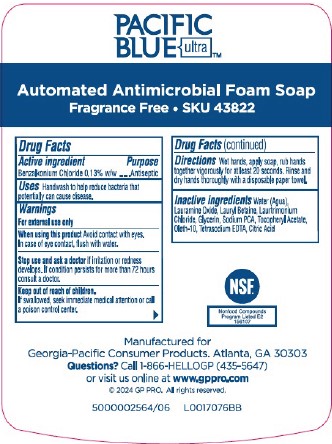 DRUG LABEL: Pacific Blue Ultra
NDC: 54622-572 | Form: SOAP
Manufacturer: Georgia-Pacific Consumer Products LP 
Category: otc | Type: HUMAN OTC DRUG LABEL
Date: 20260204

ACTIVE INGREDIENTS: BENZALKONIUM CHLORIDE 1.3 mg/1 mL
INACTIVE INGREDIENTS: .ALPHA.-TOCOPHEROL ACETATE; OLETH-10; LAURAMINE OXIDE; SODIUM PYRROLIDONE CARBOXYLATE; WATER; EDETATE SODIUM; LAURYL BETAINE; LAURTRIMONIUM CHLORIDE; CITRIC ACID MONOHYDRATE; GLYCERIN

Pacific Blue Ultra 572.001/572AD
Antimicrobial Soap – Fragrance Free and Dye Free

Claims

PACIFIC BLUE ultra™

Automated Antimicrobial Foam Soa

Fragrance Free • SKU 43822

Active ingredient

Benzalkonium chloride 0.13% w/w

Purpose

Antiseptic

Uses

Handwash to help reduce bacteria that potentially can cause disease.

Warnings

For external use only

When using this product

Avoid contact with eyes. In case of eye contact, flush with water.

Stop use and ask a doctor

if irritation or redness develops. If condition persists for more than 72 hours consult a doctor.

Keep our of reach of children.

If swallowed, seek immediate medical attention or call a poison control center.

Directions

Wet hands, apply soap, rub hands together vigorously for at least 20 seconds. Rinse and dry hands thoroughly with a disposable paper towel.

Inactive ingredients

Water (Aqua), Lauramine Oxide, Lauryl Betaine, Laurtrimonium Chloride, Glycerin, Sodium PCA, Tocopheryl Acetate, Oleth-10, Tetrasodium EDTA, Citric Acid

ADVERSE REACTION

NSF

Nonfood Compounds

Program Listed E2

156107

Manufactured for Georgia-Pacific Consumer Products. Atlanta, GA 30303

Questions? Call 1-866-HELLOGP (435-5647)

or visit us online at www.gppro.com

2024 GP PRO. All rights reserved.

Principal display panel

Antimicrobial Foam Soap

1200 mL (40.5 FL OZ)